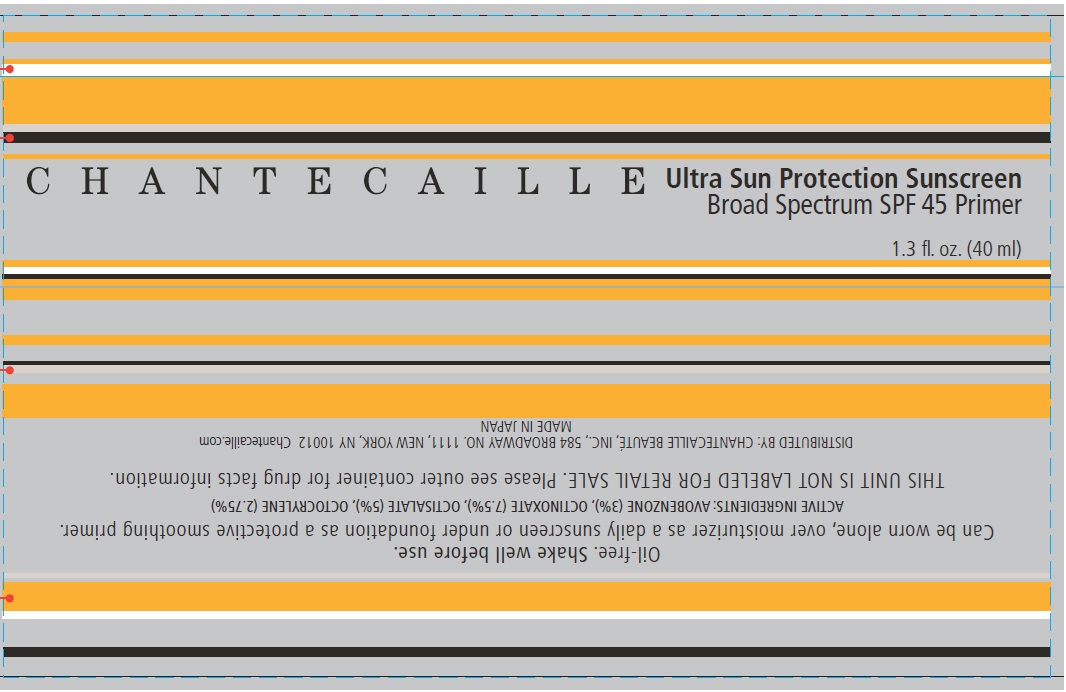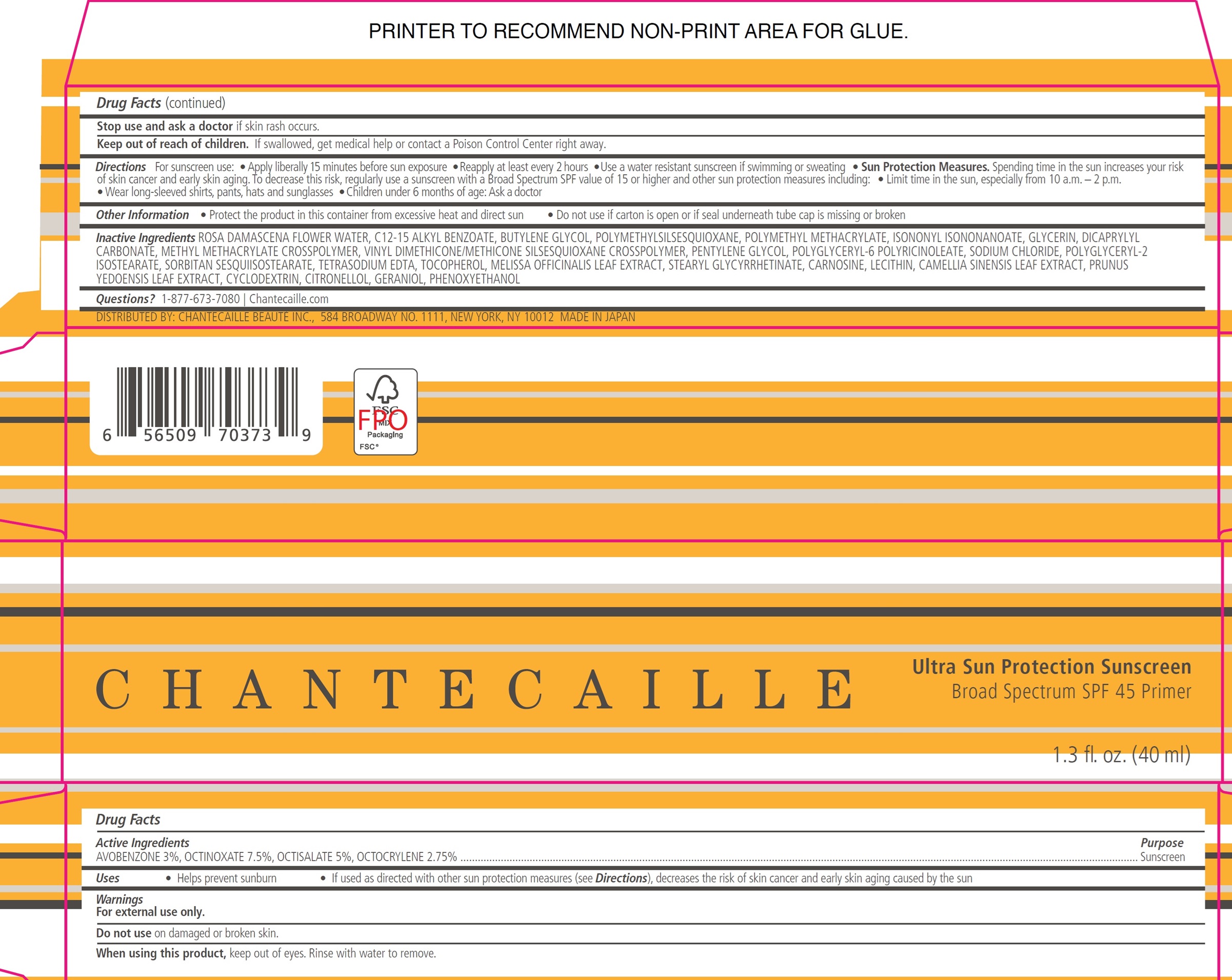 DRUG LABEL: CHANTECAILLE Ultra Sun Protection Sunscreen Broad Spectrum SPF 45
NDC: 42893-013 | Form: LOTION
Manufacturer: Chantecaille Beaute Inc
Category: otc | Type: HUMAN OTC DRUG LABEL
Date: 20241224

ACTIVE INGREDIENTS: AVOBENZONE 30 mg/1 mL; OCTINOXATE 75 mg/1 mL; OCTISALATE 50 mg/1 mL; OCTOCRYLENE 27.5 mg/1 mL
INACTIVE INGREDIENTS: POLY(METHYL METHACRYLATE; 450000 MW); ROSA X DAMASCENA FLOWER OIL; ALKYL (C12-15) BENZOATE; BUTYLENE GLYCOL; POLYMETHYLSILSESQUIOXANE (4.5 MICRONS); ISONONYL ISONONANOATE; GLYCERIN; DICAPRYLYL CARBONATE; VINYL DIMETHICONE/METHICONE SILSESQUIOXANE CROSSPOLYMER; PENTYLENE GLYCOL; POLYGLYCERYL-6 POLYRICINOLEATE; SODIUM CHLORIDE; POLYGLYCERYL-2 ISOSTEARATE; SORBITAN SESQUIISOSTEARATE; EDETATE SODIUM; TOCOPHEROL; MELISSA OFFICINALIS LEAF; STEARYL GLYCYRRHETINATE; CARNOSINE; GREEN TEA LEAF; PRUNUS X YEDOENSIS LEAF; CYCLODEXTRINS; .BETA.-CITRONELLOL, (R)-; GERANIOL; PHENOXYETHANOL

CHANTECAILLE Ultra Sun Protection Sunscreen Broad Spectrum SPF 45

Active Ingredients

AVOBENZONE 3%, OCTINOXATE 7.5%, OCTISALATE 5%, OCTOCRYLENE 2.75%

Purpose

Sunscreen

Uses

- Helps prevent sunburn
- If used as directed with other sun protection measures (see Directions), decreases the risk of skin cancer and early skin aging caused by the sun

Warnings

For external use only.

Do not use

on damaged or broken skin.

When using this product,

keep out of eyes. Rinse with water to remove.

Stop use and ask a doctor

if skin rash occurs.

Keep out of reach of children.

If swallowed, get medical help or contact a Poison Control Center right away.

Directions

For sunscreen use:

- Applyliberally 15 minutes before sun exposure
- Reapply at least every 2 hours
- Use a water resistant sunscreen if swimming or sweating
- Sun Protection Measures.Spending time in the sun increases your risk of skin cancer and early skin aging. To decrease this risk, regularly use a sunscreen with a Broad Spectrum SPF value of 15 or higher and other sun protection measures including:
- Limit time in the sun, especially from 10 a.m. – 2 p.m.
- Wear long-sleeved shirts, pants, hats and sunglasses
- Children under 6 months of age: Ask a doctor

Other Information

- Protect the product in this container from excessive heat and direct sun
- Do not use if carton is open or if seal underneath tube cap is missing or broken

Inactive Ingredients

ROSA DAMASCENA FLOWER WATER, C12-15 ALKYL BENZOATE, BUTYLENE GLYCOL, POLYMETHYLSILSESQUIOXANE, POLYMETHYL METHACRYLATE, ISONONYL ISONONANOATE, GLYCERIN, DICAPRYLYL CARBONATE, METHYL METHACRYLATE CROSSPOLYMER, VINYL DIMETHICONE/METHICONE SILSESQUIOXANE CROSSPOLYMER, PENTYLENE GLYCOL, POLYGLYCERYL-6 POLYRICINOLEATE, SODIUM CHLORIDE, POLYGLYCERYL-2 ISOSTEARATE, SORBITAN SESQUIISOSTEARATE, TETRASODIUM EDTA, TOCOPHEROL, MELISSA OFFICINALIS LEAF EXTRACT, STEARYL GLYCYRRHETINATE, CARNOSINE, LECITHIN, CAMELLIA SINENSIS LEAF EXTRACT, PRUNUS YEDOENSIS LEAF EXTRACT, CYCLODEXTRIN, CITRONELLOL, GERANIOL, PHENOXYETHANOL

Questions?

1-877-673-7080 Chantecaille.com